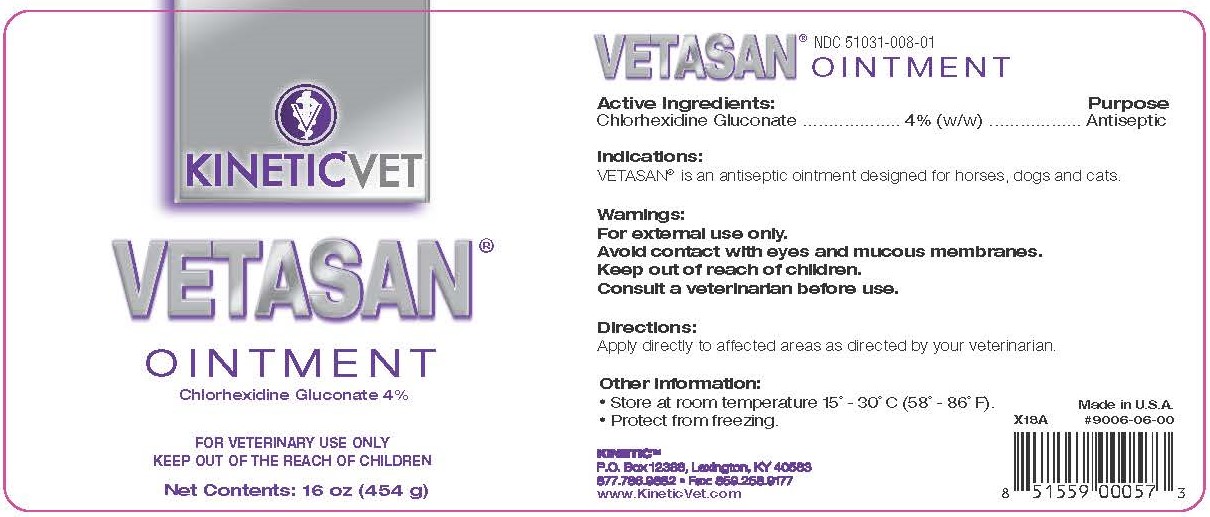 DRUG LABEL: Vetasan
NDC: 51031-008 | Form: CREAM
Manufacturer: Kinetic Technologies, LLC
Category: animal | Type: OTC ANIMAL DRUG LABEL
Date: 20231127

ACTIVE INGREDIENTS: CHLORHEXIDINE GLUCONATE 4 g/100 g

Vetasan Ointment

Active Ingredients:

Chlorhexidine Gluconate.........4% (w/w)

Purpose

Antiseptic

Indications:

VETASAN® is an antiseptic ointment designed for horses, dogs and cats.

Warnings:

For external use only.

Avoid contact with eyes and mucous membranes.

Keep out of reach of children.

Consult a veterinarian before use.

Directions:

Apply directly to affected areas as directed by your veterinarian.

Other Information:

- Store at room temperature 15° - 30°C (58° - 86°F).
- Protect from freezing.

KINETIC™

P.O. Box 12388, Lexington KY 40583

877.786.9882 • Fax: 859.258.9177

www.KineticVet.com

Made in U.S.A.

#9006-06-00

KINETIC™VET

VETASAN®

OINTMENT

Chlorhexidine Gluconate 4%

FOR VETERINARY USE ONLY

KEEP OUT OF THE REACH OF CHILDREN

Net Contents: 16 oz (454 g)